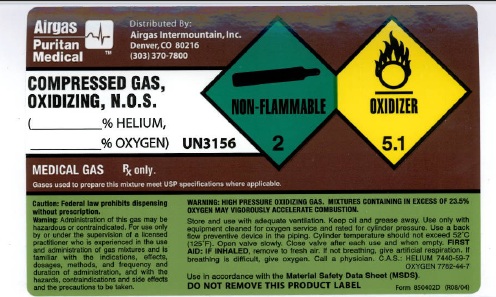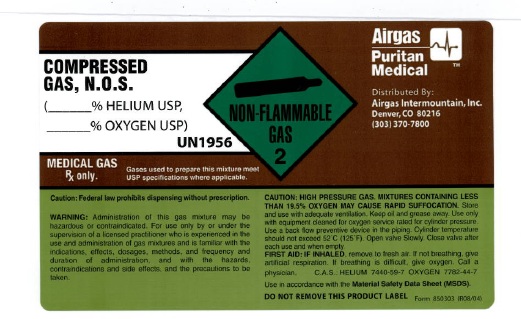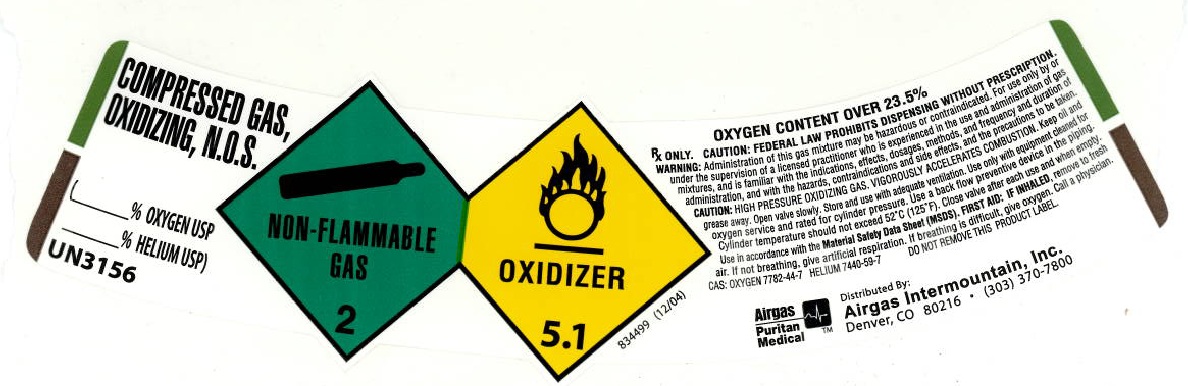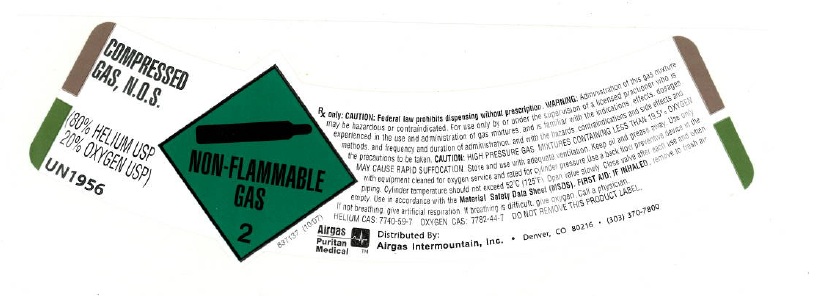 DRUG LABEL: Helium Oxygen Mixture
NDC: 58420-007 | Form: GAS
Manufacturer: Airgas Intermountain Inc
Category: prescription | Type: HUMAN PRESCRIPTION DRUG LABEL
Date: 20100622

ACTIVE INGREDIENTS: Helium 800 mL/1 L; Oxygen 200 mL/1 L

helium oxygen mixture

PACKAGE LABEL

AIRGAS PURITAN MEDICAL Distributed By: Airgas Intermountain, Inc. Denver, CO 80216 (303) 370-7800
COMPRESSED GAS, N.O.S.
(% HELIUM USP, % OXYGEN USP)
UN3156
MEDICAL GAS Rx only. Gases used to prepare this mixture meet USP specifications where applicable.
NON-FLAMMABLE 2 OXIDIZER 5.1
CAUTION: Federal law prohibits dispensing without a prescription. WARNING: Administration of this gas may be hazardous or contraindicated. For use only by or under the supervision of a licensed practitioner who is experienced in the use and administration of gas mixtures, and is familiar with the indications, effects, dosages, methods, and frequency and duration of administration, and with the hazards, contraindications and side effects, and the precautions to be taken.
CAUTION: HIGH PRESSURE OXIDIZING GAS. MIXTURES CONTAINING IN EXCESS OF 23.5% OXYGEN MAY VIGOROUSLY ACCELERATE COMBUSTION. Store and use with adequate ventilation. Keep oil and grease away. Use only with equipment cleaned for oxygen service and rated for cylinder pressure. Use a back flow preventive device in the piping. Cylinder temperature should not exceed 52oC(125oF). Open valve slowly. Close valve after each use and when empty.
FIRST AID: IF INHALED, remove to fresh air. If not breathing, give artificial respiration. If breathing is difficult, give oxygen. Call a physician. C.A.S. : HELIUM 7440-59-7 OXYGEN 7782-44-7 Use in accordance with the Material Safety Data Sheet (MSDS).
DO NOT REMOVE THIS PRODUCT LABEL.
Form 850402D (R08/04)

PACKAGE LABEL

COMPRESSED GAS, N.O.S.
(% HELIUM USP, % OXYGEN USP)
UN1956
MEDICAL GAS Rx only. Gases used to prepare this mixture meet USP specifications where applicable.
NON-FLAMMABLE 2
AIRGAS PURITAN MEDICAL Distributed By: Airgas Intermountain, Inc. Denver, CO 80216 (303) 370-7800
CAUTION: Federal law prohibits dispensing without a prescription. WARNING: Administration of this gas may be hazardous or contraindicated. For use only by or under the supervision of a licensed practitioner who is experienced in the use and administration of gas mixtures, and is familiar with the indications, effects, dosages, methods, and frequency and duration of administration, and with the hazards, contraindications and side effects, and the precautions to be taken.
CAUTION: HIGH PRESSURE OXIDIZING GAS. MIXTURES CONTAINING LESS THAN 19.5% OXYGEN MAY CAUSE RAPID SUFFOCATION. Store and use with adequate ventilation. Keep oil and grease away. Use only with equipment cleaned for oxygen service and rated for cylinder pressure. Use a back flow preventive device in the piping. Cylinder temperature should not exceed 52oC(125oF). Open valve slowly. Close valve after each use and when empty.
FIRST AID: IF INHALED, remove to fresh air. If not breathing, give artificial respiration. If breathing is difficult, give oxygen. Call a physician. C.A.S. : HELIUM 7440-59-7 OXYGEN 7782-44-7 Use in accordance with the Material Safety Data Sheet (MSDS).
DO NOT REMOVE THIS PRODUCT LABEL.
Form 850303 (R08/04)

PACKAGE LABEL

COMPRESSED GAS, N.O.S.
(% HELIUM USP, % OXYGEN USP)
UN3156
NON-FLAMMABLE 2 OXIDIZER 5.1
834499 (12/04)
OXYGEN CONTENT OVER 23.5%
Rx only.
CAUTION: Federal law prohibits dispensing without a prescription. WARNING: Administration of this gas mixture may be hazardous or contraindicated. For use only by or under the supervision of a licensed practitioner who is experienced in the use and administration of gas mixtures, and is familiar with the indications, effects, dosages, methods, and frequency and duration of administration, and with the hazards, contraindications and side effects, and the precautions to be taken.
CAUTION: HIGH PRESSURE OXIDIZING GAS. VIGOROUSLY ACCELERATES COMBUSTION. Keep oil and grease away. Open valve slowly. Store and use with adequate ventilation. Use only with equipment cleaned for oxygen service and rated for cylinder pressure. Use a back flow preventive device in the piping. Cylinder temperature should not exceed 52oC(125oF). Close valve after each use and when empty. Use in accordance with the Material Safety Data Sheet (MSDS).
FIRST AID: IF INHALED, remove to fresh air. If not breathing, give artificial respiration. If breathing is difficult, give oxygen. Call a physician. CAS. : OXYGEN 7782-44-7 HELIUM 7440-59-7
DO NOT REMOVE THIS PRODUCT LABEL.
AIRGAS PURITAN MEDICAL Distributed By: Airgas Intermountain, Inc. Denver, CO 80216 (303) 370-7800

PACKAGE LABEL

COMPRESSED GAS, N.O.S.
(80% HELIUM USP, 20 % OXYGEN USP)
UN1956
NON-FLAMMABLE 2
837137 (10/07)
Rx only. CAUTION: Federal law prohibits dispensing without a prescription. WARNING: Administration of this gas mixture may be hazardous or contraindicated. For use only by or under the supervision of a licensed practitioner who is experienced in the use and administration of gas mixtures, and is familiar with the indications, effects, dosages, methods, and frequency and duration of administration, and with the hazards, contraindications and side effects, and the precautions to be taken.
CAUTION: HIGH PRESSURE GAS MIXTURES CONTAINING LESS THAN 19.5% OXYGEN MAY CAUSE RAPID SUFFOCATION. Store and use with adequate ventilation. Keep oil and grease away. Use only with equipment cleaned for oxygen service and rated for cylinder pressure. Use a back flow preventive device in the piping. Cylinder temperature should not exceed 52oC(125oF). Open valve slowly. Close valve after each use and when empty. Use in accordance with the Material Safety Data Sheet (MSDS).
FIRST AID: IF INHALED, remove to fresh air. If not breathing, give artificial respiration. If breathing is difficult, give oxygen. Call a physician. HELIUM CAS: 7440-59-7 OXYGEN CAS: 7782-44-7
DO NOT REMOVE THIS PRODUCT LABEL.
AIRGAS PURITAN MEDICAL Distributed By: Airgas Intermountain, Inc. Denver, CO 80216 (303) 370-7800